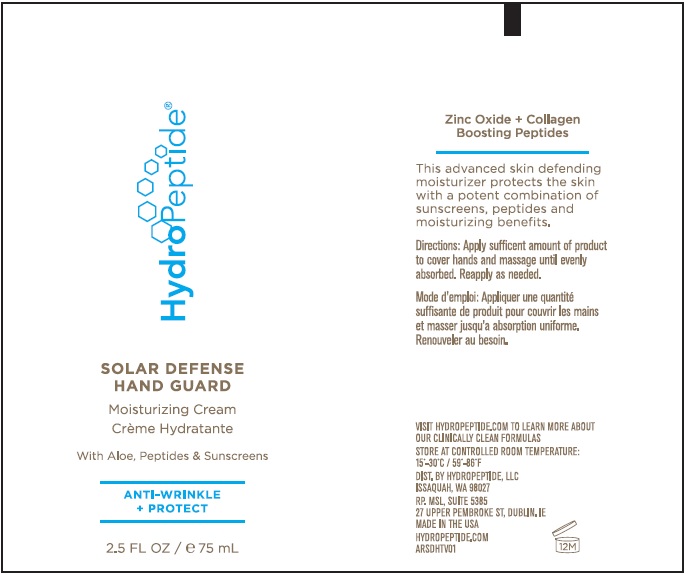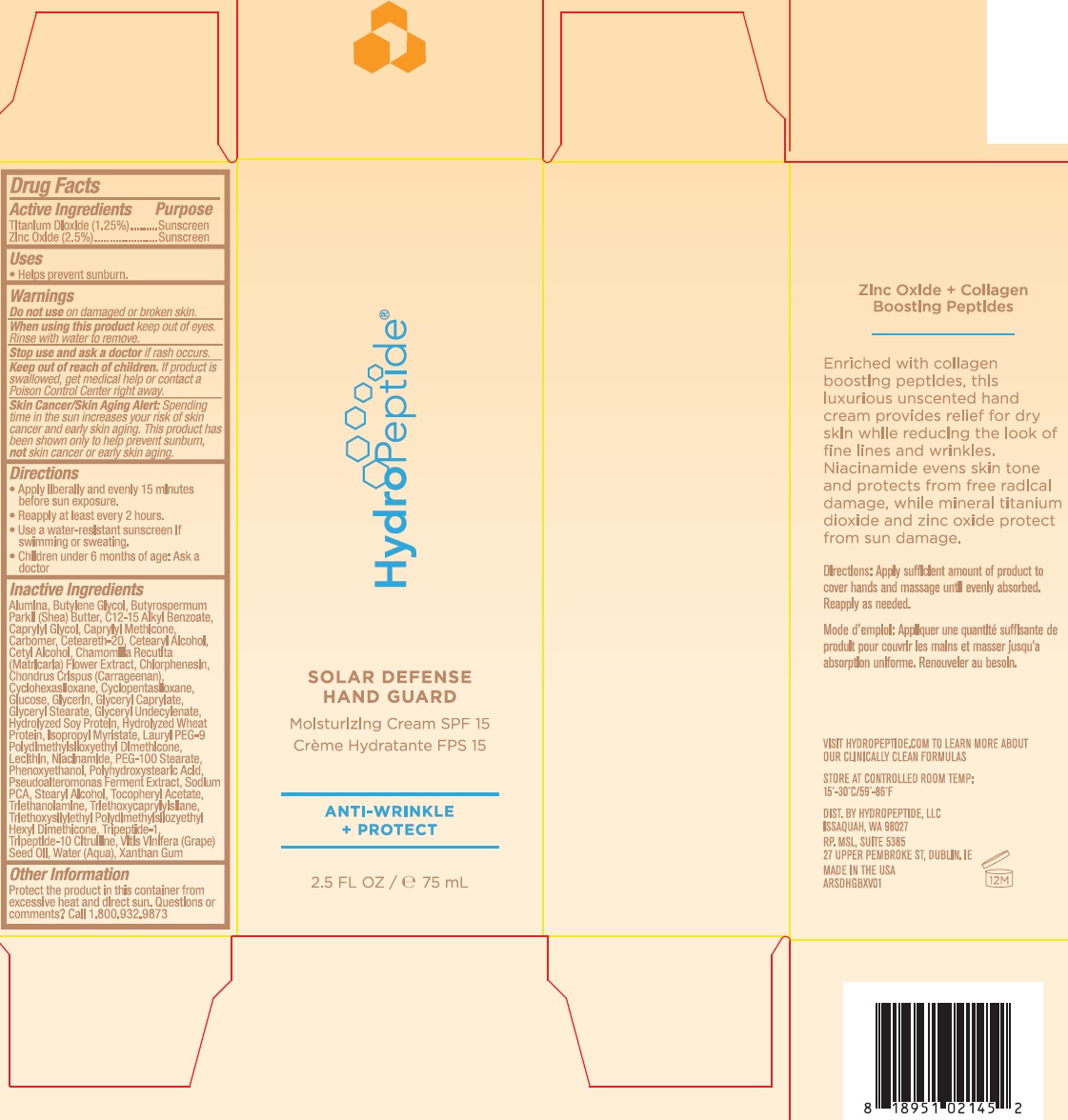 DRUG LABEL: HydroPeptide Solar Defense Hand Guard
NDC: 60934-011 | Form: CREAM
Manufacturer: HydroPeptide LLC
Category: otc | Type: HUMAN OTC DRUG LABEL
Date: 20211018

ACTIVE INGREDIENTS: TITANIUM DIOXIDE 12.5 mg/1 mL; ZINC OXIDE 25 mg/1 mL
INACTIVE INGREDIENTS: ALUMINUM OXIDE; BUTYLENE GLYCOL; SHEA BUTTER; ALKYL (C12-15) BENZOATE; CAPRYLYL GLYCOL; CAPRYLYL TRISILOXANE; CARBOMER HOMOPOLYMER, UNSPECIFIED TYPE; POLYOXYL 20 CETOSTEARYL ETHER; CETOSTEARYL ALCOHOL; CETYL ALCOHOL; CHAMOMILE; CHLORPHENESIN; CHONDRUS CRISPUS CARRAGEENAN; CYCLOMETHICONE 6; CYCLOMETHICONE 5; ANHYDROUS DEXTROSE; GLYCERIN; GLYCERYL CAPRYLATE; GLYCERYL MONOSTEARATE; GLYCERYL 1-UNDECYLENATE; HYDROLYZED SOY PROTEIN (ENZYMATIC; 2000 MW); HYDROLYZED WHEAT PROTEIN (ENZYMATIC; 3000 MW); ISOPROPYL MYRISTATE; LAURYL PEG-9 POLYDIMETHYLSILOXYETHYL DIMETHICONE; NIACINAMIDE; PEG-100 STEARATE; PHENOXYETHANOL; SODIUM PYRROLIDONE CARBOXYLATE; STEARYL ALCOHOL; .ALPHA.-TOCOPHEROL ACETATE; TROLAMINE; TRIETHOXYCAPRYLYLSILANE; TRIETHOXYSILYLETHYL POLYDIMETHYLSILOXYETHYL HEXYL DIMETHICONE; PREZATIDE; TRIPEPTIDE-10 CITRULLINE; GRAPE SEED OIL; WATER; XANTHAN GUM

HydroPeptide Solar Defense Hand Guard

Active Ingredients

Titanium Dioxide 1.25%, Zinc Oxide 2.5%.

Purpose

Sunscreen

Uses

• Helps prevent sunburn.

Warnings

Skin Cancer/Skin Aging Alert: Spending time in the sun increases your risk of skin cancer and early skin aging. This product has been shown only to help prevent sunburn, not skin cancer or early skin aging.

Do not use

on damaged or broken skin.

When using this product

keep out of eyes. Rinse with water to remove.

Stop use and ask a doctor

if rash occurs.

Keep out of reach of children.

If product is swallowed, get medical help or contact a Poison Control Center right away.

Directions

• Apply liberally and evenly 15 minutes before sun exposure.
• Reapply at least every 2 hours.
• Use a water-resistant sunscreen if swimming or sweating.
• Children under 6 months of age: Ask a doctor

Inactive Ingredients

Alumina, Butylene Glycol, Butyrospermum Parkii (Shea) Butter, C12-15 Alkyl Benzoate, Caprylyl Glycol, Caprylyl Methicone, Carbomer, Ceteareth-20, Cetearyl Alcohol, Cetyl Alcohol, Chamomilla Recutita (Matricaria) Flower Extract, Chlorphenesin, Chondrus Crispus (Carrageenan), Cyclohexasiloxane, Cyclopentasiloxane, Glucose, Glycerin, Glyceryl Caprylate, Glyceryl Stearate, Glyceryl Undecylenate, Hydrolyzed Soy Protein, Hydrolyzed Wheat Protein, Isopropyl Myristate, Lauryl PEG-9 Polydimethylsiloxyethyl Dimethicone, Lecithin, Niacinamide, PEG-100 Stearate, Phenoxyethanol, Polyhydroxystearic Acid, Pseudoalteromonas Ferment Extract, Sodium PCA, Stearyl Alcohol, Tocopheryl Acetate, Triethanolamine, Triethoxycaprylylsilane, Triethoxysilylethyl Polydimethylsilozyethyl Hexyl Dimethicone, Tripeptide-1, Tripeptide-10 Citrulline, Vitis Vinifera (Grape) Seed Oil, Water (Aqua), Xanthan Gum